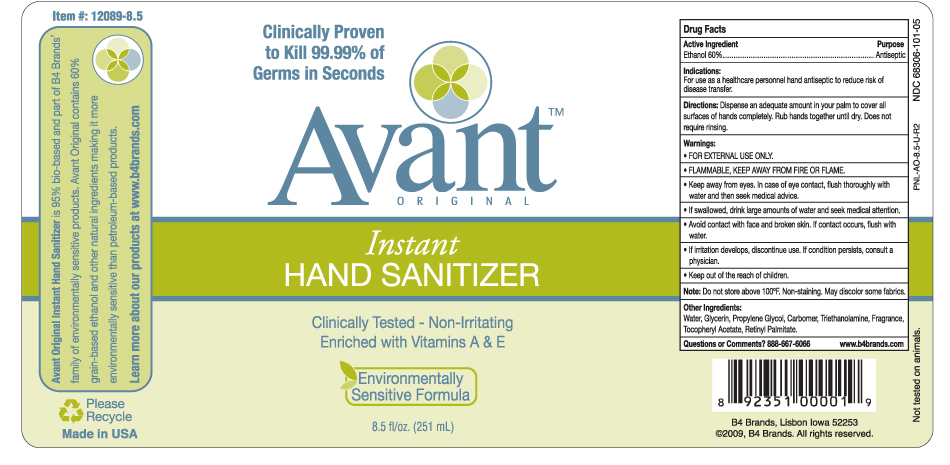 DRUG LABEL: Avant Original Instant Hand Sanitizer
NDC: 68306-101 | Form: GEL
Manufacturer: B4 Ventures LLC
Category: otc | Type: HUMAN OTC DRUG LABEL
Date: 20101005

ACTIVE INGREDIENTS: Alcohol 60 mL/100 mL
INACTIVE INGREDIENTS: Water; Glycerin; Propylene Glycol; Trolamine; Carbomer 1342; .ALPHA.-TOCOPHEROL ACETATE, D-; VITAMIN A PALMITATE

B4 Brands: Avant Original Instant Hand Sanitizer

Bio-Based Hand Sanitizer

Avant Original Instant Hand Sanitizer is bio-based and part of B4 Brands' family of environmentally sensitive products. Avant Original contains 60% grain based ethanol and other natural ingredients, making it more environmentally sensitive than petroleum based products.

Learn more about our products at www.b4brands.com

ACTIVE INGREDIENT

Ethanol 60%

Purpose

Antiseptic

Warnings:

- FOR EXTERNAL USE ONLY.
- FLAMMABLE, KEEP AWAY FROM FIRE OR FLAME.
- Keep away from eyes. In case of eye contact, flush thoroughly with water and then seek medical advice.
- If swallowed, drink large amounts of water and seek medical attention.
- Avoid contact with face and broken skin. If contact occurs, flush with water.

STOP USE

- If irritation develops, discontinue use. If condition persists, consult a physician.

- Keep out of reach of children.

STORAGE AND HANDLING

Do not store above 100 degrees F. Non-staining. May discolor some fabrics.

Other Ingredients:

Water, Glycerin, Propylene Glycol, Carbomer, Triethanolamine, Fragrance, Tocopheryl Acetate, Retinyl Palmitate.

QUESTIONS

Question or Comments? 888-667-6066 www.b4brands.com

PACKAGE LABEL

251 ml Pump Bottle

DOSAGE AND ADMINISTRATION

Dispense an adequate amount in your palm to cover all surfaces of hands completely. Rub hands together until dry. Does not require rinsing.

INDICATIONS AND USAGE

For hand sanitizing when soap and water are not available.